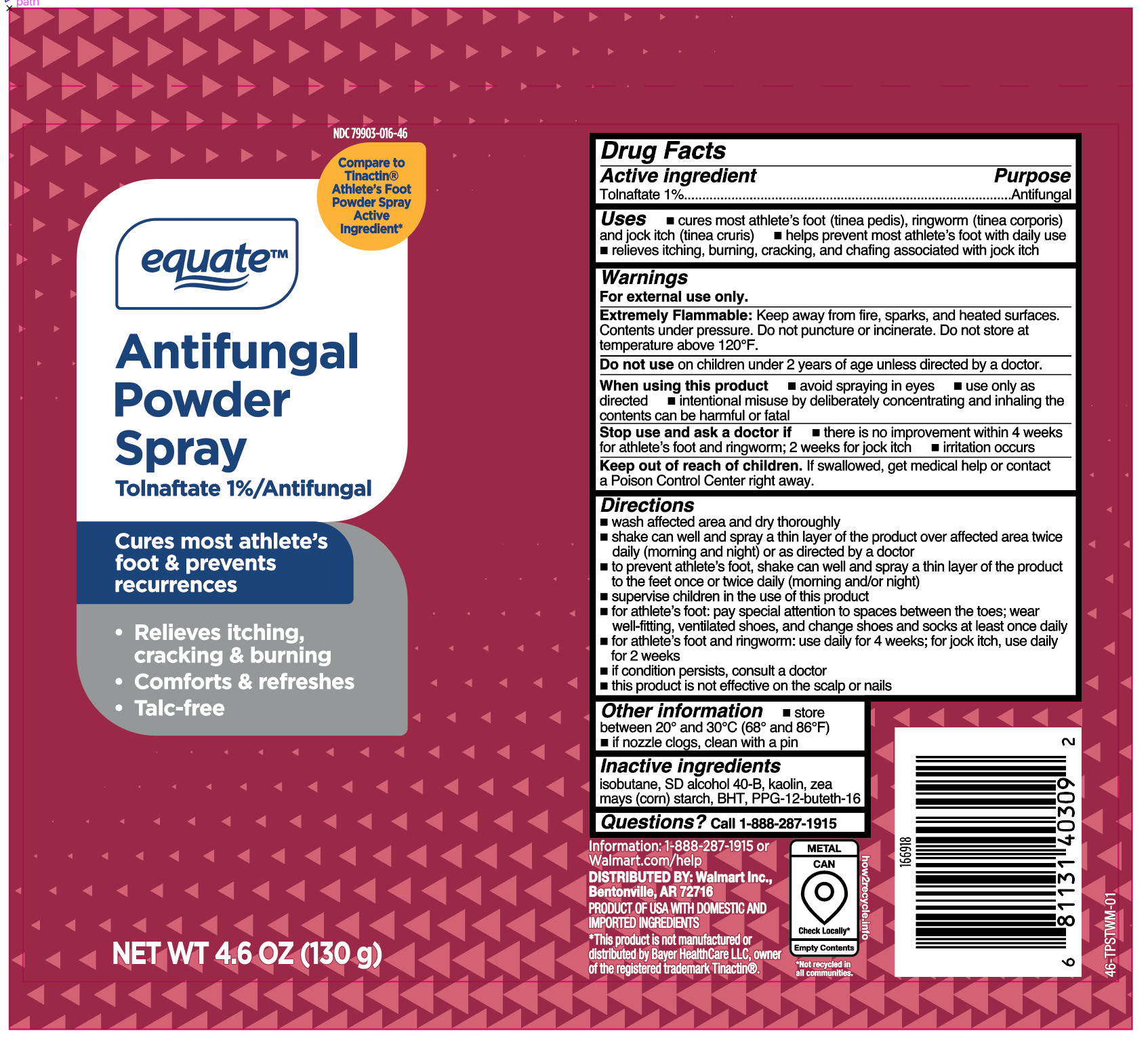 DRUG LABEL: Tolnafate
NDC: 79903-016 | Form: AEROSOL, SPRAY
Manufacturer: Wal-Mart Stores, Inc
Category: otc | Type: HUMAN OTC DRUG LABEL
Date: 20260128

ACTIVE INGREDIENTS: TOLNAFTATE 1.3 g/130 g
INACTIVE INGREDIENTS: BUTYLATED HYDROXYTOLUENE; ISOBUTANE; KAOLIN; PPG-12-BUTETH-16; ALCOHOL; ZEA MAYS SUBSP. MAYS WHOLE

Equate Tolnaftate 1% Powder Spray

Active ingredient

Tolnaftate 1%

Purpose

Antifungal

Uses

- cures most athlete's foot (tinea pedis), ringworm (tinea corporis) and jock itch (tinea cruris)
- helps prevent most athlete's foot with daily use
- relieves itching, burning, cracking, and chafing associated with jock itch

Warnings

For external use only.

Extremely Flammable:

Keep away from fire, sparks, and heated surfaces. Contents under pressure. Do not puncture or incinerate. Do not store at
temperature above 120°F.

Do not use

on children under 2 years of age unless directed by a doctor.

When using this product

- avoid spraying in eyes
- use only as directed
- intentional misuse by deliberately concentrating and inhaling the contents can be harmful or fatal

Stop use and ask a doctor if

- there is no improvement within 4 weeks for athlete's foot and ringworm; 2 weeks for jock itch
- irritation occurs

Keep out of reach of children.

If swallowed, get medical help or contact a Poison Control Center right away.

Directions

- wash affected area and dry thoroughly
- shake can well and spray a thin layer of the product over affected area twice daily (morning and night) or as directed by a doctor
- to prevent athlete's foot, shake can well and spray a thin layer of the product to the feet once or twice daily (morning and/or night)
- supervise children in the use of this product
- for athlete's foot: pay special attention to spaces between the toes; wear well-fitting, ventilated shoes, and change shoes and socks at least once daily
- for athlete's foot and ringworm: use daily for 4 weeks; for jock itch, use daily for 2 weeks
- if condition persists, consult a doctor
- this product is not effective on the scalp or nails

Other information

- store between 20º and 30ºC (68º and 86ºF)
- if nozzle clogs, clean with a pin

Inactive ingredients

isobutane, SD alcohol 40-B, kaolin, zea mays (corn) starch, BHT, PPG-12-buteth-16

Questions?

1-888-287-1915

RECENT MAJOR CHANGES

.

Principal Display Panel

equate

Antifungal

Powder

Spray

Tolnaftate 1% Antifungal

Cures most athlete's
foot & prevents
recurrences

- Relieves itching,

cracking & burning

- Comforts & refreshes
- Talc-free

NET WT 4.6 OZ (130g)